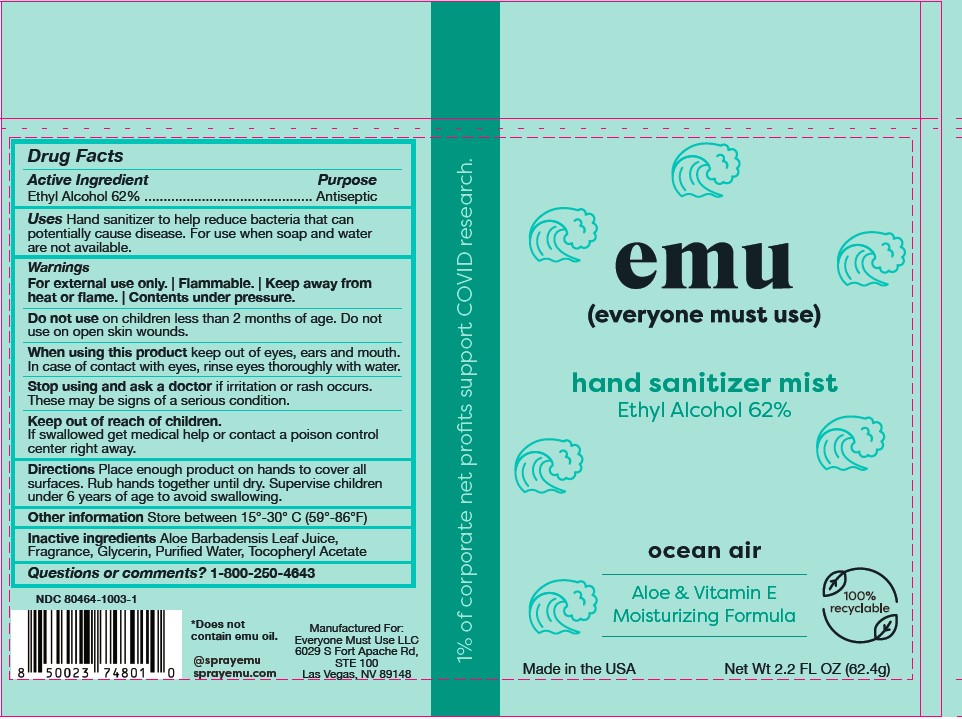 DRUG LABEL: EMU Hand Sanitizer Mist Ocean Air
NDC: 80464-1003 | Form: SPRAY
Manufacturer: Everyone Must Use, LLC
Category: otc | Type: HUMAN OTC DRUG LABEL
Date: 20231222

ACTIVE INGREDIENTS: ALCOHOL 0.62 g/1 g
INACTIVE INGREDIENTS: ALOE VERA LEAF; GLYCERIN; ALPHA-TOCOPHEROL ACETATE; WATER

EMU Hand Sanitizer Mist Ocean Air

Purpose

Antiseptic, Hand Sanitizer

Drug Facts

For external use only. | Flammable. | Keep away from heat or flame. | Contents under pressure.

Active Ingredient | Purpose
Ethyl Alcohol 62% | Antiseptic

Uses

Hand Sanitizer to help reduce bacteria that potentially can cause disease. For use when soap and water are not available.

Warnings

For external use only. | Flammable. | Keep away from heat or flame. | Contents under pressure.

Do not use

on children less than 2 months of age. Do not use on open skin wounds.

When using this product keep out of eyes, ears and mouth. In case of contact with eyes, rinse eyes thoroughly with water.

Stop use and ask a doctor if irritation or rash occurs. These may be signs of a serious condition.

Keep out of reach of children. If swallowed, get medical help or contact a Poison Control Center right away.

Directions

Place enough product on hands to cover all surfaces. Rub hands together until dry. Supervise children under 6 years of age to avoid swallowing.

Other information

Store between 15°-30° C (59°-86°F)

Inactive ingredients

Aloe Barbadensis Leaf Juice, Fragrance, Glycerin, Purified Water, Tocopheryl Acetate

Questions or comments?

1-800-250-4643

Package Label - Principal Display Panel

Net Wt 2.2 FL OZ (62.4g) NDC: 80464-1003-1